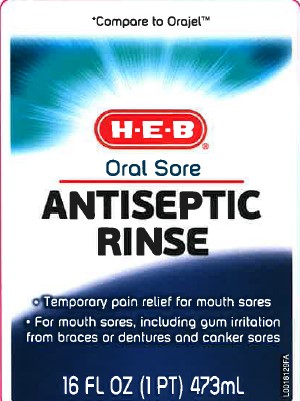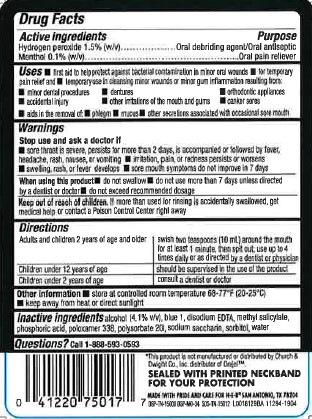 DRUG LABEL: Oral Sore Antiseptic
NDC: 37808-024 | Form: LIQUID
Manufacturer: H E B
Category: otc | Type: HUMAN OTC DRUG LABEL
Date: 20260224

ACTIVE INGREDIENTS: HYDROGEN PEROXIDE 15 mg/1 mL; MENTHOL 1 mg/1 mL
INACTIVE INGREDIENTS: ALCOHOL; FD&C BLUE NO. 1; EDETATE DISODIUM ANHYDROUS; METHYL SALICYLATE; PHOSPHORIC ACID; POLOXAMER 338; POLYSORBATE 20; SACCHARIN SODIUM; SORBITOL; WATER

HEB 024.000/024AB
Oral Sore Antiseptic Rinse

active ingredients

Hydrogen peroxide 1.5% (w/v)

Menthol 0.1% (w/v)

purpose

Oral debriding agent/Oral antiseptic
Oral pain reliever

uses

▪ first aid to help protect against bacterial contamination in minor oral wounds
▪ for temporary pain relief and ▪ temporary use in cleansing minor wounds or minor gum inflammation resulting from: ▪ minor dental procedures ▪ dentures ▪ orthodontic appliances ▪ accidental injury ▪ other irritations of the mouth and gums ▪ canker sores
▪ aids in the removal of: ▪ phlegm ▪ mucus ▪ other secretions associated with occasional sore mouth

warnings

for this product

Stop use and ask a doctor if

▪ sore throat is severe, persists for more than 2 days, is accompanied or followed by fever, headache, rash, nausea, or vomiting
▪ irritation, pain, or redness persists or worsens
▪ swelling, rash, or fever develops
▪ sore mouth symptoms do not improve in 7 days

When using this product

- do not swallow
- do not use more than 7 days unless directed by a dentist or doctor
- do not exceed recommended dosage

Keep out of reach of children

If more than used for rinsing is accidentally swallowed, get medical help or contact a Poison Control Center right away

directions

Adults and children 2 years of age and older - swish two teaspoons (10 mL) around the mouth for at least 1 minute, then spit out; use up to 4 times daily or as directed by a dentist or physician

Children under 12 years of age - should be supervised in the use of the product

Children under 2 years of age - consult a dentist or doctor

other information

- store at controlled room temperature 68-77°F (20-25°C)
- keep away from heat or direct sunlight

inactive ingredients

alcohol (4.1% v/v), blue 1, disodium EDTA, methyl salicylate, phosphoric acid, poloxamer 338, polysorbate 20, sodium saccharin, sorbitol, water

Questions?

Call 1-888-593-0593

ADVERSE REACTION

*This product is not manufactured or distributed by Church & Dwight Co., Inc distributor of Orajel.

SEALED WITH PRINTED NACKBAND FOR YOUR PROTECTION

Made with pride and care for HEB San Antonio, TX 78204

DSP-TN-15000 DSP-MO-34 SDS-TN-15012

Principal display panel

*Compare to Orajel™

HEB

Oral Sore

Antiseptic Rinse

- Temporary pain relief for mouth sores
- For mouth sores, including gum irritation from braces or dentures and canker sores

16 FL OZ (1 PT) 473 mL